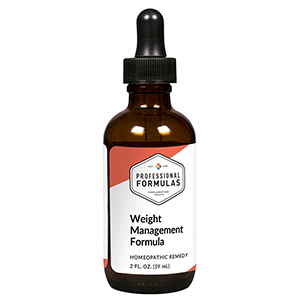 DRUG LABEL: Weight Management Formula
NDC: 63083-7534 | Form: LIQUID
Manufacturer: Professional Complementary Health Formulas
Category: homeopathic | Type: HUMAN OTC DRUG LABEL
Date: 20190815

ACTIVE INGREDIENTS: GARCINIA GUMMI-GUTTA FRUIT 2 [hp_X]/59 mL; ARTEMISIA CINA PRE-FLOWERING TOP 3 [hp_X]/59 mL; FUCUS VESICULOSUS 3 [hp_X]/59 mL; ALPHA LIPOIC ACID 3 [hp_X]/59 mL; AMMONIUM CARBONATE 6 [hp_X]/59 mL; SEMECARPUS ANACARDIUM JUICE 6 [hp_X]/59 mL; NERIUM OLEANDER WHOLE 6 [hp_X]/59 mL; PHOSPHORUS 6 [hp_X]/59 mL; DELPHINIUM STAPHISAGRIA SEED 6 [hp_X]/59 mL; SODIUM CHLORIDE 6 [hp_X]/59 mL; BOS TAURUS HYPOTHALAMUS 6 [hp_X]/59 mL; BOS TAURUS PITUITARY GLAND, POSTERIOR 6 [hp_X]/59 mL; THYROID, UNSPECIFIED 6 [hp_X]/59 mL; ANTIMONY TRISULFIDE 8 [hp_X]/59 mL; AMMONIUM BROMIDE 12 [hp_X]/59 mL; LYCOPODIUM CLAVATUM SPORE 12 [hp_X]/59 mL; OYSTER SHELL CALCIUM CARBONATE, CRUDE 30 [hp_X]/59 mL; OLEA EUROPAEA FLOWER 30 [hp_X]/59 mL
INACTIVE INGREDIENTS: ALCOHOL; WATER

IWM

ACTIVE INGREDIENTS

Garcinia cambogia 2X
Cina 3X
Fucus vesiculosus 3X
Alpha lipoicum acidum 3X, 6X, 12X
Ammonium carbonicum 6X
Anacardium orientale 6X
Oleander 6X
Phosphorus 6X
Staphysagria 6X
Cell salt combination (cell salts 1-12) 6X, 12X, 30X
Hypothalamus 6X, 12X, 30X
Pituitary 6X, 12X, 30X
Thyroid 6X, 12X, 30X
Antimonium crudum 8X
Ammonium bromatum 12X
Lycopodium clavatum 12X
Calcarea carbonica 30X
Olive flower essence 30X

QUESTIONS

Professional Formulas

PO Box 2034 Lake Oswego, OR 97035

INDICATIONS

For improving weight loss efforts by temporarily relieving increased appetite or cravings, occasional headache, and irritability due to a restricted diet.*

PURPOSE

*Claims based on traditional homeopathic practice, not accepted medical evidence. Not FDA evaluated.

WARNINGS

In case of overdose, get medical help or contact a poison control center right away.

Keep out of the reach of children.

PREGNANCY OR BREAST FEEDING

If pregnant or breastfeeding, ask a healthcare professional before use.

DIRECTIONS

Place drops under tongue 30 minutes before/after meals. Adults and children 12 years and over: Take 10 drops up to 3 times per day. Consult a physician for use in children under 12 years of age.

OTHER INFORMATION

Tamper resistant. If seal is broken, do not use. After opening, close container tightly and store at room temperature away from heat.

INACTIVE INGREDIENTS

20% ethanol, purified water.

LABEL

Est 1985

Professional Formulas

Complementary Health

Weight Management Formula

Homeopathic Remedy

2 FL. OZ. (59 mL)